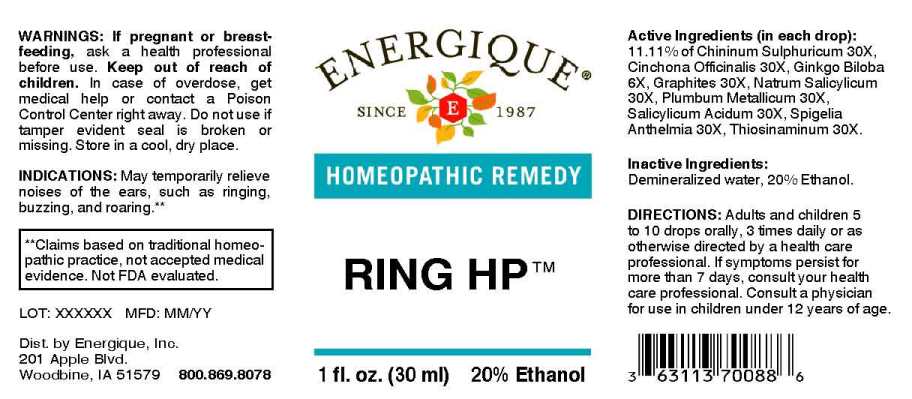 DRUG LABEL: Ring HP
NDC: 44911-0626 | Form: LIQUID
Manufacturer: Energique, Inc.
Category: homeopathic | Type: HUMAN OTC DRUG LABEL
Date: 20230822

ACTIVE INGREDIENTS: GINKGO 6 [hp_X]/1 mL; QUININE SULFATE 30 [hp_X]/1 mL; CINCHONA OFFICINALIS BARK 30 [hp_X]/1 mL; GRAPHITE 30 [hp_X]/1 mL; SODIUM SALICYLATE 30 [hp_X]/1 mL; LEAD 30 [hp_X]/1 mL; SALICYLIC ACID 30 [hp_X]/1 mL; SPIGELIA ANTHELMIA WHOLE 30 [hp_X]/1 mL; ALLYLTHIOUREA 30 [hp_X]/1 mL
INACTIVE INGREDIENTS: WATER; ALCOHOL

DRUG FACTS:

ACTIVE INGREDIENTS:

(in each drop): 11.11% of Chininum Sulphuricum 30X, Cinchona Officinalis 30X, Ginkgo Biloba 6X, Graphites 30X, Natrum Salicylicum 30X, Plumbum Metallicum 30X, Salicylicum Acidum 30X, Spigelia Anthelmia 30X, Thiosinaminum 30X.

INDICATIONS:

May temporary relief noises of the ears, such as ringing, buzzing, roaring.**

**Claims based on traditional homeopathic practice, not accepted medical evidence. Not FDA evaluated.

WARNINGS:

If pregnant or breast-feeding, ask a health professional before use.

Keep out of reach of children. In case of overdose, get medical help or contact a Poison Control Center right away.

Do not use if tamper evident seal is broken or missing. Store in a cool, dry place.

KEEP OUT OF REACH OF CHILDREN:

In case of overdose, get medical help or contact a Poison Control Center right away.

DIRECTIONS

Adults and children 5 to 10 drops orally, 3 times daily or as otherwise directed by a health care professional. If symptoms persist for more than 7 days, consult your health care professional. Consult a physician for use in children under 12 years of age.

INDICATIONS:

May temporary relief noises of the ears, such as ringing, buzzing, roaring.**

**Claims based on traditional homeopathic practice, not accepted medical evidence. Not FDA evaluated.

INACTIVE INGREDIENTS:

Demineralized water, 20% Ethanol.

QUESTIONS:

Dist. by Energique, Inc.

201 Apple Blvd

Woodbine, IA 51579

800-869-8078

PACKAGE LABEL DISPLAY:

ENERGIQUE

since 1987

HOMEOPATHIC REMEDY

Ring HP

1 fl. oz. (30 ml)